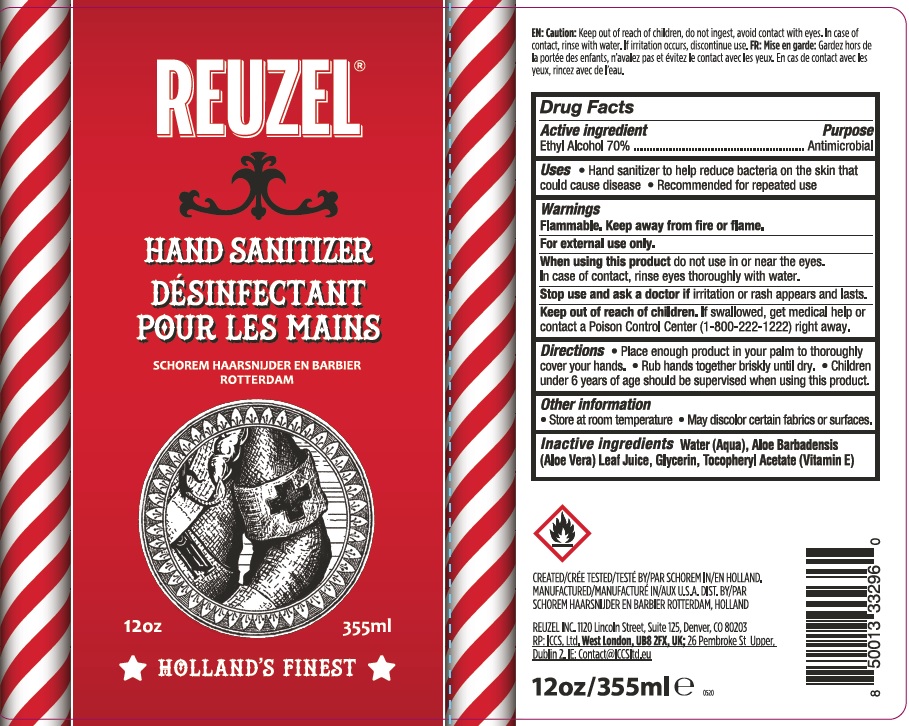 DRUG LABEL: Hand Sanitizer
NDC: 77911-002 | Form: SOLUTION
Manufacturer: Reuzel, Inc.
Category: otc | Type: HUMAN OTC DRUG LABEL
Date: 20200527

ACTIVE INGREDIENTS: ALCOHOL 70 mL/100 mL
INACTIVE INGREDIENTS: GLYCERIN; ALOE VERA LEAF; WATER; .ALPHA.-TOCOPHEROL ACETATE

Hand Sanitizer

Active Ingredient(s)

Alcohol 70% Purpose: Antimicrobial

Purpose

Antimicrobial

Use

- Hand Sanitizer to help reduce bacteria on the skin that could cause disease.
- Recommended for repeated use

Keep out of reach of children. If swallowed, get medical help or contact a Poison Control Center (1-800-222-1222) right away.

Stop use and ask a doctor if irritation or rash appears and lasts.

Warnings

Flammable. Keep away from fire or flame.

For external use only.

When using this product do not use in or near the eyes.

In case of contact with eyes, rinse eyes thoroughly with water

Directions

- Place enough product in your palm to thoroughly cover your hands. Rub hands together briskly until dry.
- Children under 6 years of age should be supervised when using this product.

Other information

- Store at room temperature
- May discolor certain fabrics or surface

Inactive ingredients

Water (Aqua), Aloe Barbadensis (Aloe Vera) Leaf Juice, Glycerin, Tocopheryl Acetate (Vitamin E)

Package Label - Principal Display Panel

Reuzel

Hand Sanitizer

Desifectant Pour Les Mains

Schorem Haarsnijder en Barbier

Rotterdam

12 oz 355 ml